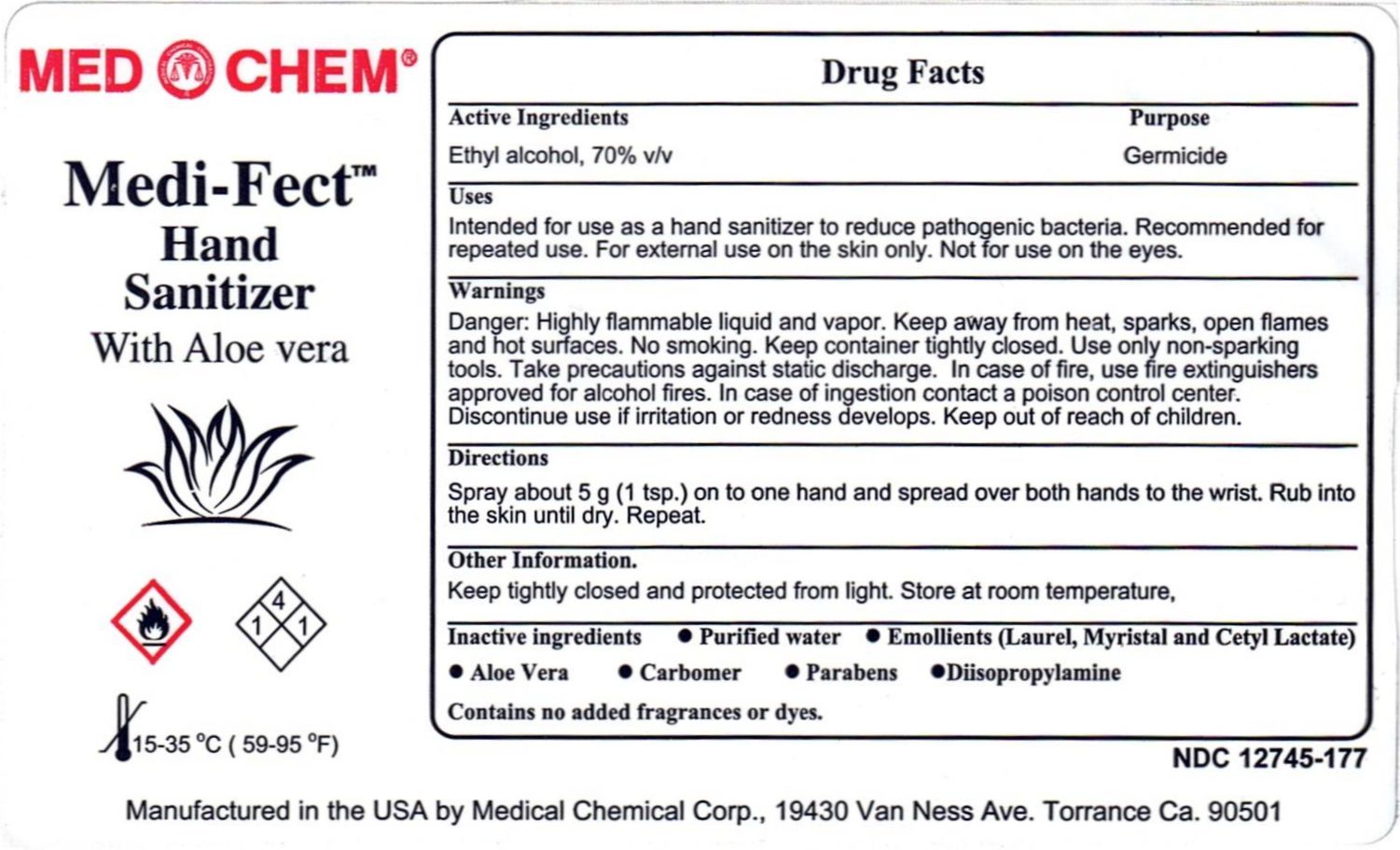 DRUG LABEL: Medi Fect
NDC: 12745-177 | Form: LIQUID
Manufacturer: Medical Chemical Corporation
Category: otc | Type: HUMAN OTC DRUG LABEL
Date: 20250731

ACTIVE INGREDIENTS: ALCOHOL 59.86 g/100 mL; DIAZOLIDINYL UREA 1 g/100 mL
INACTIVE INGREDIENTS: CARBOMER HOMOPOLYMER TYPE C 0.5 g/100 mL; POLYSORBATE 80 0.5 g/100 mL; ALOE VERA LEAF 0.5 g/100 mL; DIISOPROPYLAMINE 0.505 g/100 mL; WATER

Medi Fect Label

PURPOSE

Indications for use: For hospital and professional use only. Medi-Fect is intended to be used as a hand-wash to reduce bacteria that can potentially cause disease. Recommended for repeated use.

ACTIVE INGREDIENT

Ingredients: 70% v/v ethyl alcohol, propylene glycol, emolients (polysorbate 80, cetyl alcohol, acetylated lanolin alcohol), carbomer, diazolidinyl urea, methyl paraben, aloe vera and propyl paraben. Contains emollients and skin conditioners. Contains no added fragrance or dyes.

INACTIVE INGREDIENT

Ingredients: 70% v/v ethyl alcohol, propylene glycol, emolients (polysorbate 80, cetyl alcohol, acetylated lanolin alcohol), carbomer, diazolidinyl urea, methyl paraben, aloe vera and propyl paraben. Contains emollients and skin conditioners. Contains no added fragrance or dyes.

KEEP OUT OF REACH OF CHILDREN

Warnings: Flammable, keep away from fire or flame. For external use only. Do no use in the eyes. Discontinue use if irritation or redness develops. Keep out of reach of children. In case of ingestion contact poison control center immediately.

WARNINGS

Warnings: Flammable, keep away from fire or flame. For external use only. Do no use in the eyes. Discontinue use if irritation or redness develops. Keep out of reach of children. In case of ingestion contact poison control center immediately.

DOSAGE AND ADMINISTRATION

Directions: Place a 'palmful' (about 5 g) of product in one hand. Spread on both hands and rub into the skin until dry (approximately 1 to 2 minutes). Place a smaller amount (2.5 grams) into one hand, spread over both hands to wrist, and rub into skin until dry (approximately 30 seconds).

INDICATIONS AND USAGE

Indications for use: For hospital and professional use only. Medi-Fect is intended to be used as a hand-wash to reduce bacteria that can potentially cause disease. Recommended for repeated use.

PACKAGE LABEL

medifectlabel.jpg